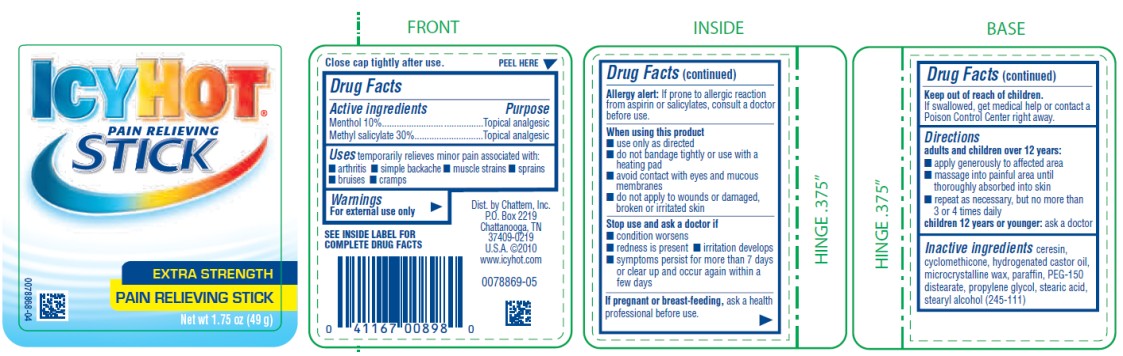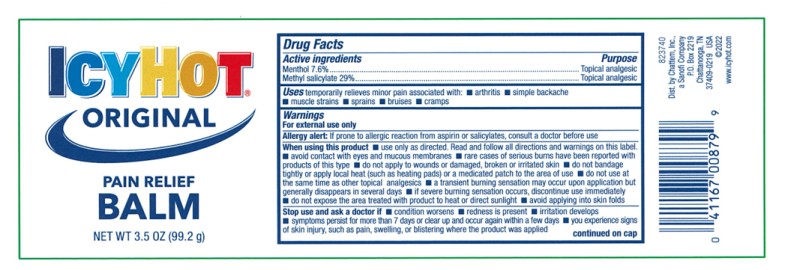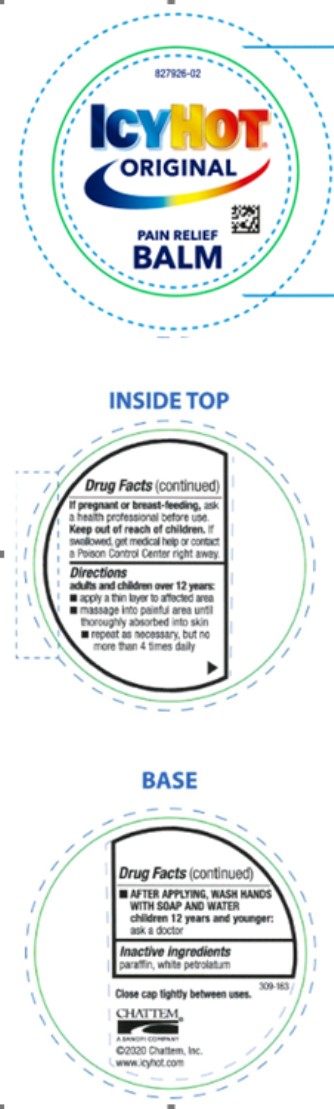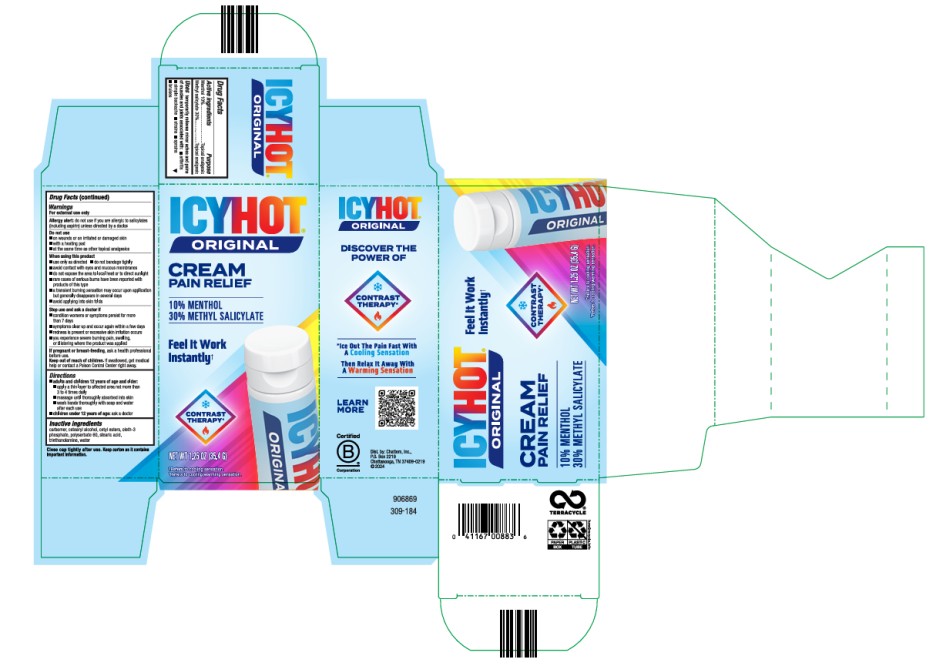 DRUG LABEL: Icy Hot
NDC: 41167-0089 | Form: STICK
Manufacturer: Chattem, Inc.
Category: otc | Type: HUMAN OTC DRUG LABEL
Date: 20250501

ACTIVE INGREDIENTS: MENTHOL 10 g/100 g; METHYL SALICYLATE 30 g/100 g
INACTIVE INGREDIENTS: CERESIN; CYCLOMETHICONE; HYDROGENATED CASTOR OIL; MICROCRYSTALLINE WAX; PARAFFIN; PEG-150 DISTEARATE; PROPYLENE GLYCOL; STEARIC ACID; STEARYL ALCOHOL

Icy Hot

ICYHOT® PAIN RELIEVING STICK
Drug Facts

Active ingredient

Menthol 10%

Methyl salicylate 30%

Purpose

Topical analgesic

Uses

temporarily relieves minor pain associated with:

- arthritis
- simple backache
- muscle strains
- sprains
- bruises
- cramps

Warnings

For external use only

SEE INSIDE LABEL FOR COMPLETE DRUG FACTS

Allergy Alert: If prone to allergic reaction from aspirin or salicylates, consult a doctor before use.

When using this product

■ use only as directed. Read and follow all directions and warnings on this label.

■ avoid contact with eyes and mucous membranes

■ rare cases of serious burns have been reported with products of this type

■ do not apply to wounds or damaged, broken or irritated skin

■ do not bandage tightly or apply local heat (such as heating pads) or a medicated patch to the area of use

■ a transient burning sensation may occur upon application but generally disappears in several days

■ if severe burning sensation occurs, discontinue use immediately

■ do not expose the area treated with product to heat or direct sunlight

Stop use and ask a doctor if

- condition worsens
- redness is present
- irritation develops
- symptoms persist for more than 7 days or clear up and occur again within a few days

If pregnant or breast-feeding,

ask a health care professional before use.

Keep out of reach of children.

If swallowed, get medical help or contact a Poison Control Center right away.

Directions

adults and children over 12 years:

- apply a thin layer to affected area
- massage into painful area until thoroughly absorbed into skin
- repeat as necessary, but not more than 4 times daily

children 12 years or younger: ask a doctor

Inactive ingredients

ceresin, cyclomethicone, hydrogenated castor oil, microcrystalline wax, paraffin, PEG-150 distearate, propylene glycol, stearic acid, stearyl alcohol (245-111)

ICYHOT® PAIN RELIEVING BALM
Drug Facts

Active ingredient

Menthol 7.6%

Methyl salicylate 29%

Purpose

Topical analgesic

Uses

temporarily relieves minor pain associated with:

- arthritis
- simple backache
- muscle strains
- sprains
- bruises
- cramps

Warnings

For external use only

Allergy alert: if prone to allergic reaction from aspirin or salicylates, consult a doctor before use

When using this product

■ use only as directed. Read and follow all directions and warnings on this label.

■ avoid contact with eyes and mucous membranes

■ rare cases of serious burns have been reported with products of this type

■ do not apply to wounds or damaged, broken or irritated skin

■ do not bandage tightly or apply local heat (such as heating pads) or a medicated patch to the area of use

■ do not use at the same time as other topical analgesics

■ a transient burning sensation may occur upon application but generally disappears in several days

■ if severe burning sensation occurs, discontinue use immediately

■ do not expose the area treated with product to heat or direct sunlight

■ avoid applying into skin folds

Stop use and ask a doctor if

■ condition worsens

■ redness is present

■ irritation develops

■ symptoms persist for more than 7 days or clear up and occur again within a few days

■ you experience signs of skin injury, such as pain, swelling, or blistering where the product was applied

If pregnant or breast-feeding,

ask a health professional before use.

Keep out of reach of children.

If swallowed, get medical help or contact a Poison Control Center right away.

Directions

adults and children over 12 years:

■ apply a thin layer to affected area

■ massage into painful area until thoroughly absorbed into skin

■ repeat as necessary, but no more than 4 times daily

■ AFTER APPLYING, WASH HANDS WITH SOAP AND WATER

children 12 years or younger: ask a doctor

Inactive ingredients

paraffin, white petrolatum

ICYHOT® PAIN RELIEVING CREAM
Drug Facts

Active ingredient

Menthol 10%

Methyl salicylate 30%

Purpose

Topical analgesic

Uses

temporarily relieves minor aches and pains of muscles and joints associated with:

- arthritis
- simple backache
- strains
- sprains
- bruises

Warnings

For external use only

Allergy alert: do not use if you are allergic to salicylates (including aspirin) unless directed by a doctor.

Do not use

■ on wounds or on irritated or damaged skin

■ with a heating pad

■ at the same time as other topical analgesics

When using this product

■ use only as directed

■ do not bandage tightly

■ avoid contact with eyes and mucous membranes

■ do not expose the area to local heat or to direct sunlight

■ rare cases of serious burns have been reported with products of this type

■ a transient burning sensation may occur upon application but generally disappears in several days

■ avoid applying into skin folds

Stop use and ask a doctor if

■ condition worsens or symptoms persist for more than 7 days

■ symptoms clear up and occur again within a few days

■ redness is present or excessive skin irritation occurs

■ you experience severe burning pain, swelling, or blistering where the product was applied

If pregnant or breast-feeding,

ask a health professional before use.

Keep out of reach of children.

If swallowed, get medical help or contact a Poison Control Center right away.

Directions

■ adults and children 12 years of age and older:
■ apply a thin layer to affected area not more than 3 to 4 times daily

■ massage until thoroughly absorbed into skin

■ wash hands thoroughly with soap and water after each use
■ children under 12 years of age: ask a doctor

Inactive ingredients

carbomer, cetearyl alcohol, cetyl esters, oleth-3 phosphate, polysorbate 60, stearic acid, triethanolamine, water

Close cap tightly after use.

PRINCIPAL DISPLAY PANEL

ICYHOT® PAIN RELIEVING STICK
EXTRA STRENGTH
PAIN RELIEVING STICK
Net wt 1.75 oz (49 g)

PRINCIPAL DISPLAY PANEL

ICY HOT®
ORIGINAL
PAIN RELIEF
BALM
NET WT 3.5 OZ (99.2 g)

PRINCIPAL DISPLAY PANEL

ICYHOT®
ORIGINAL
CREAM
PAIN RELIEF
NET WT 1.25 oz (35.4 G)